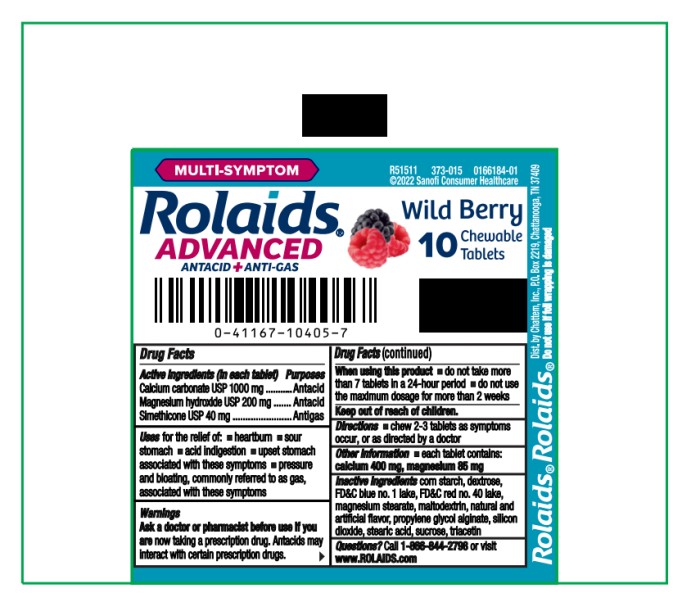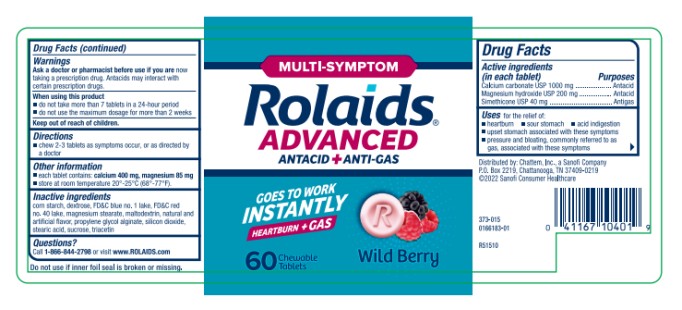 DRUG LABEL: Rolaids Advanced Antacid Anti-gas Wild Berry
NDC: 41167-1041 | Form: TABLET, CHEWABLE
Manufacturer: Chattem, Inc.
Category: otc | Type: HUMAN OTC DRUG LABEL
Date: 20260114

ACTIVE INGREDIENTS: CALCIUM CARBONATE 1000 mg/1 1; MAGNESIUM HYDROXIDE 200 mg/1 1; DIMETHICONE 40 mg/1 1
INACTIVE INGREDIENTS: STARCH, CORN; DEXTROSE; FD&C BLUE NO. 1; FD&C RED NO. 40; MAGNESIUM STEARATE; MALTODEXTRIN; PROPYLENE GLYCOL ALGINATE; SILICON DIOXIDE; STEARIC ACID; SUCROSE; TRIACETIN

Rolaids Advanced Antacid Anti-Gas Wild Berry

Rolaids Advanced Antacid plus Anti-Gas Chewable Tablets

(Wild Berry)

Drug Facts

Active ingredients (in each tablet)

Calcium carbonate USP 1000 mg

Magnesium hydroxide USP 200 mg

Simethicone USP 40 mg

Purposes

Antacid

Antacid

Antigas

Uses

for the relief of: ■ heartburn ■ sour stomach ■ acid indigestion

■ upset stomach associated with these symptoms

■ pressure and bloating, commonly referred to as gas, associated with these symptoms

Warnings

Ask a doctor or pharmacist before use if you are

now taking a prescription drug. Antacids may interact with certain prescription drugs.

When using this product

■ do not take more than 7 tablets in a 24-hour period

■ do not use the maximum dosage for more than 2 weeks

Directions

■ chew 2-3 tablets as symptoms occur, or as directed by a doctor

Other information

■ each tablet contains: calcium 400 mg, magnesium 85 mg

■ store at room temperature 20°-25°C (68°-77°F).

Inactive ingredients

corn starch, dextrose, FD&C blue no. 1 lake, FD&C red no. 40 lake, magnesium stearate, maltodextrin, natural and artificial flavor, propylene glycol alginate, silicon dioxide, stearic acid, sucrose, triacetin

Questions?

Call 1-866-844-2798 or visit www. ROLAIDS.com

Keep carton as it contains important product information.

PRINCIPAL DISPLAY PANEL

MULTI-SYMPTOM
Rolaids®
ADVANCED
ANTACID + ANTI-GAS
10 Chewable Tablets
Wild Berry

PRINCIPAL DISPLAY PANEL

MULTI-SYMPTOM
Rolaids®
ADVANCED
ANTACID + ANTI-GAS
60 Chewable Tablets
Wild Berry